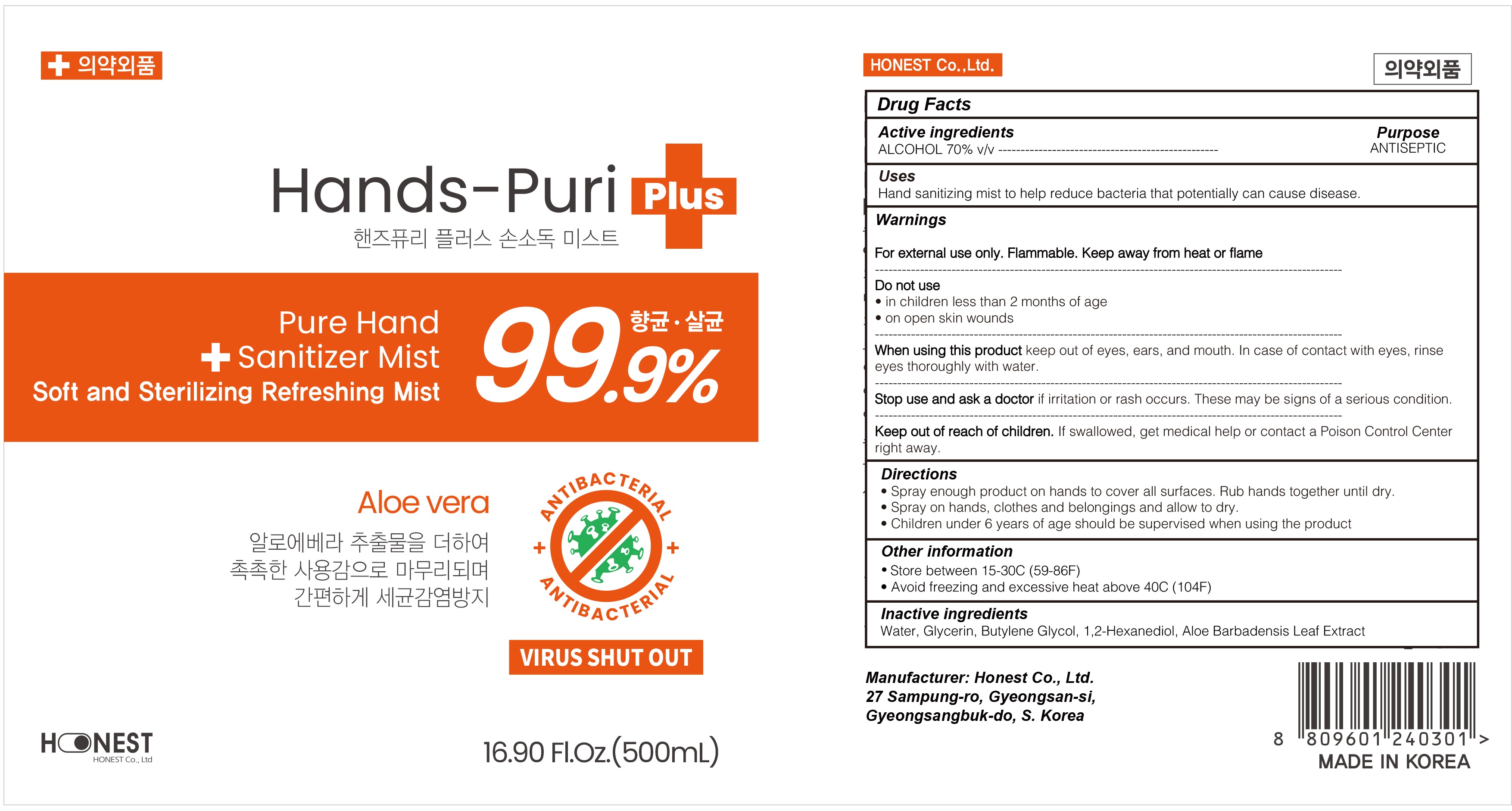 DRUG LABEL: Hands Puri Plus Hand Sanitizing Mist
NDC: 76904-080 | Form: SPRAY
Manufacturer: Honest Co., Ltd.
Category: otc | Type: HUMAN OTC DRUG LABEL
Date: 20200511

ACTIVE INGREDIENTS: ALCOHOL 350 mL/500 mL
INACTIVE INGREDIENTS: Water; Glycerin; Butylene Glycol; 1,2-Hexanediol; ALOE VERA LEAF

ACTIVE INGREDIENT

Active ingredients: ALCOHOL 70% v/v

INACTIVE INGREDIENT

Inactive ingredients:

Water, Glycerin, Butylene Glycol, 1,2-Hexanediol, Aloe Barbadensis Leaf Extract

PURPOSE

Purpose: ANTISEPTIC

WARNINGS

For external use only. Flammable. Keep away from heat or flame
--------------------------------------------------------------------------------------------------------
Do not use
• in children less than 2 months of age
• on open skin wounds
--------------------------------------------------------------------------------------------------------
When using this product keep out of eyes, ears, and mouth. In case of contact with eyes, rinse eyes thoroughly with water.
--------------------------------------------------------------------------------------------------------
Stop use and ask a doctor if irritation or rash occurs. These may be signs of a serious condition.

KEEP OUT OF REACH OF CHILDREN

If swallowed, get medical help or contact a Poison Control Center right away.

Uses

Hand sanitizing mist to help reduce bacteria that potentially can cause disease.

Directions

• Spray enough product on hands to cover all surfaces. Rub hands together until dry.
• Spray on hands, clothes and belongings and allow to dry.
• Children under 6 years of age should be supervised when using the product

Other information

• Store between 15-30C (59-86F)
• Avoid freezing and excessive heat above 40C (104F)